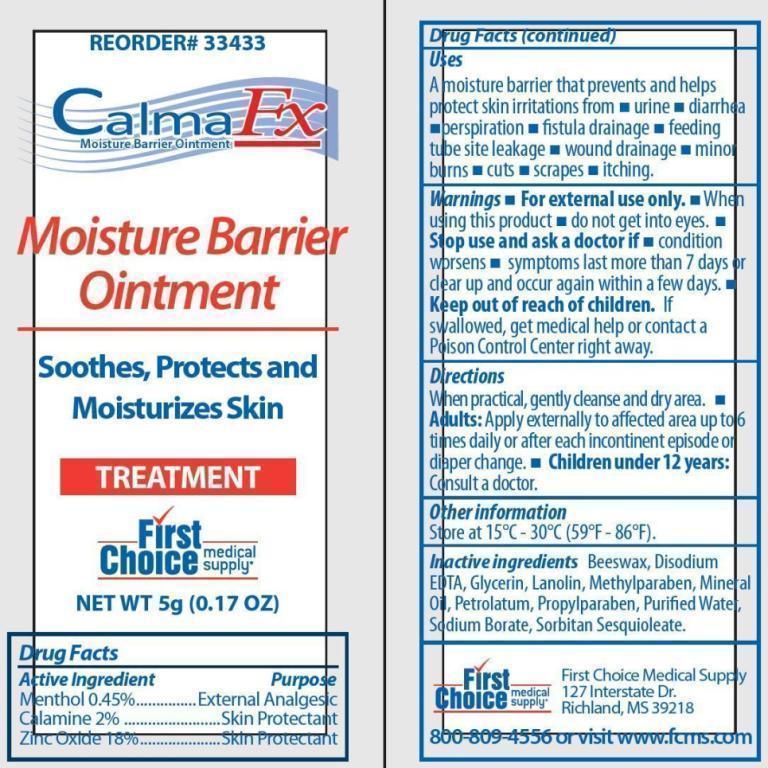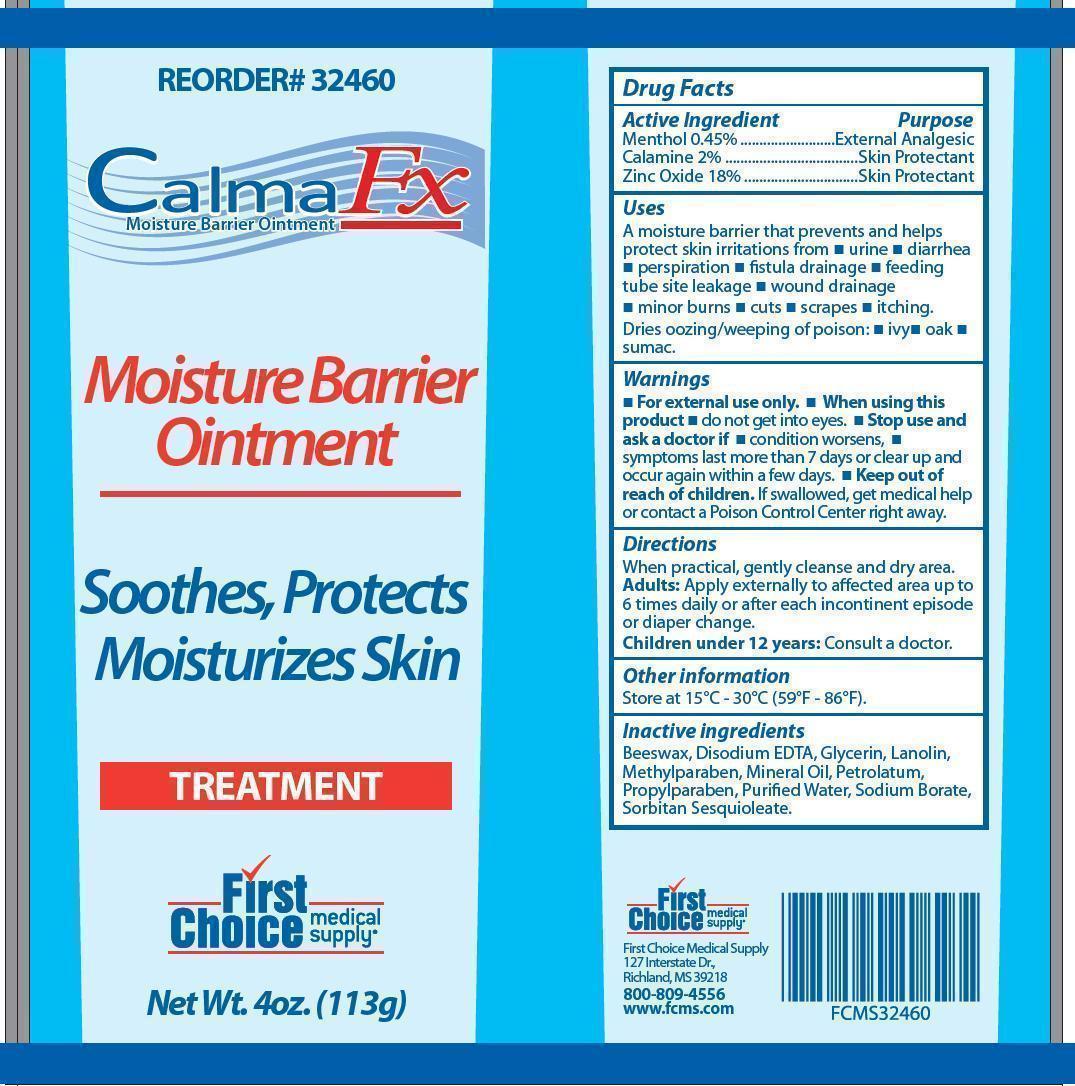 DRUG LABEL: CalmaFX
NDC: 75904-3246 | Form: OINTMENT
Manufacturer: First Choice Medical Supply
Category: otc | Type: HUMAN OTC DRUG LABEL
Date: 20130322

ACTIVE INGREDIENTS: MENTHOL 4.5 mg/1 g; FERRIC OXIDE RED 20 mg/1 g; ZINC OXIDE 180 mg/1 g
INACTIVE INGREDIENTS: YELLOW WAX; EDETATE DISODIUM; GLYCERIN; LANOLIN; METHYLPARABEN; MINERAL OIL; PETROLATUM; PROPYLPARABEN; WATER; SODIUM BORATE; SORBITAN SESQUIOLEATE

CalmaFX Moisture Barrier Ointment Drug Facts

Active Ingredients

Menthol 0.45%

Calamine 2%

Zinc Oxide 18%

Purpose

External Analgesic, Skin Protectant

Uses

A moisture barrier that prevents and helps protect skin irritations from

- urine
- diarrhea
- perspiration
- fistula drainage
- feeding tube site leakage
- wound drainage
- minor burns
- cuts
- scrapes
- itching

Warnings

- For external use only.
- When using this product
- do not get into eyes.

Stop use and ask doctor if :

- condition worsens
- symptoms last more than 7 days or clear up and occur again within a few days.

- Keep out of reach of children. If swallowed, get medical help or contact a Poison Control Center right away.

Directions

When practical, gently cleanse and dry area.

- Adults: Apply externally to affected area up to 6 times daily or after each incontinent episode or diaper change.
- Children under 12 years: Consult a doctor.

Other Information

Store at 15-30°C (59-86°F)

Inactive Ingredients:

Beeswax, Disodium EDTA, Glycerin, Lanolin, Methylparaben, Mineral Oil, Petrolatum, Propylparaben, Purified Water, Sodium Borate, Sorbitan Sesquioleate

Questions or Comments?

First Choice Medical Supply

127 Interstate Dr.

Richland, MS 39218

800-809-4556 or visit www.fcms.com

Item # 33433

Images of representative artwork

CalmafxSachet.jpg calmafxtube.jpg